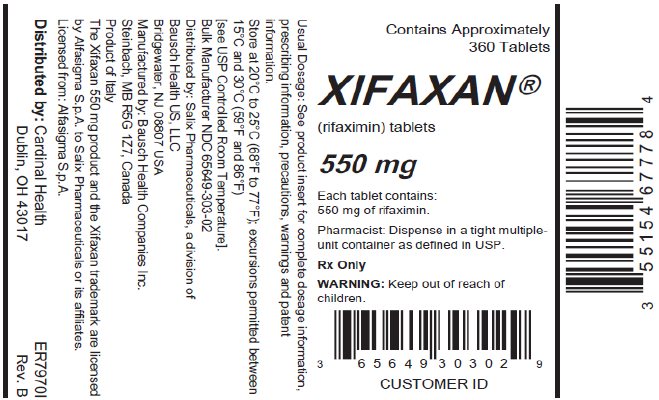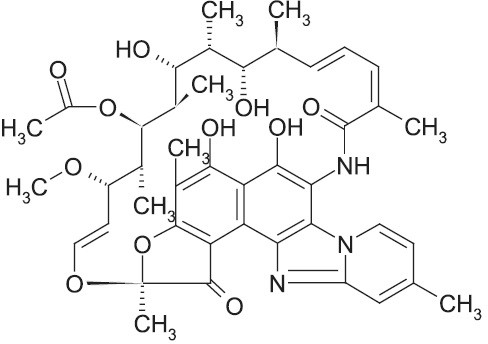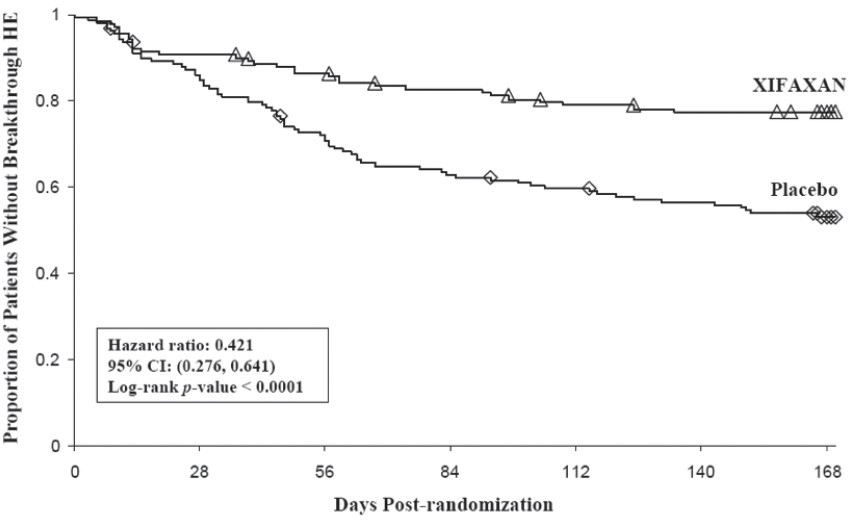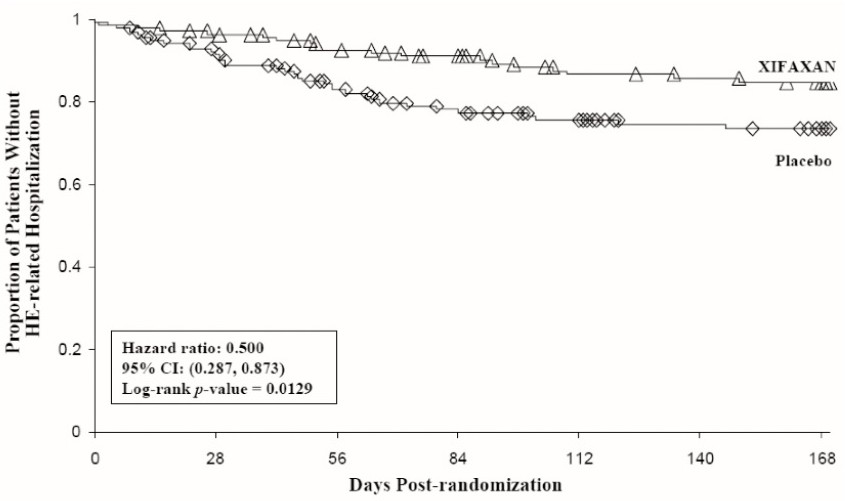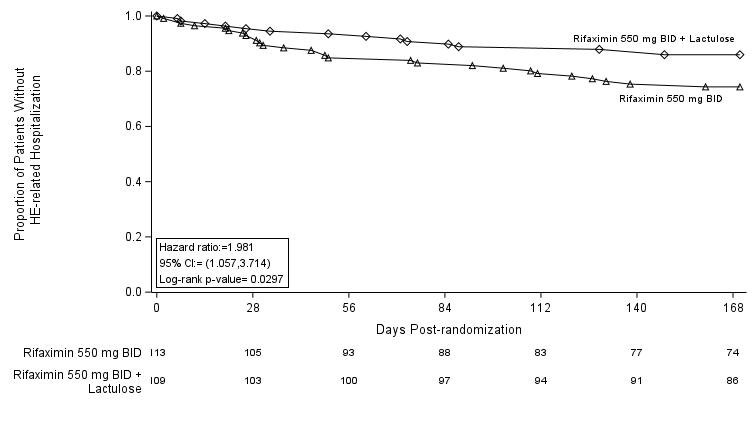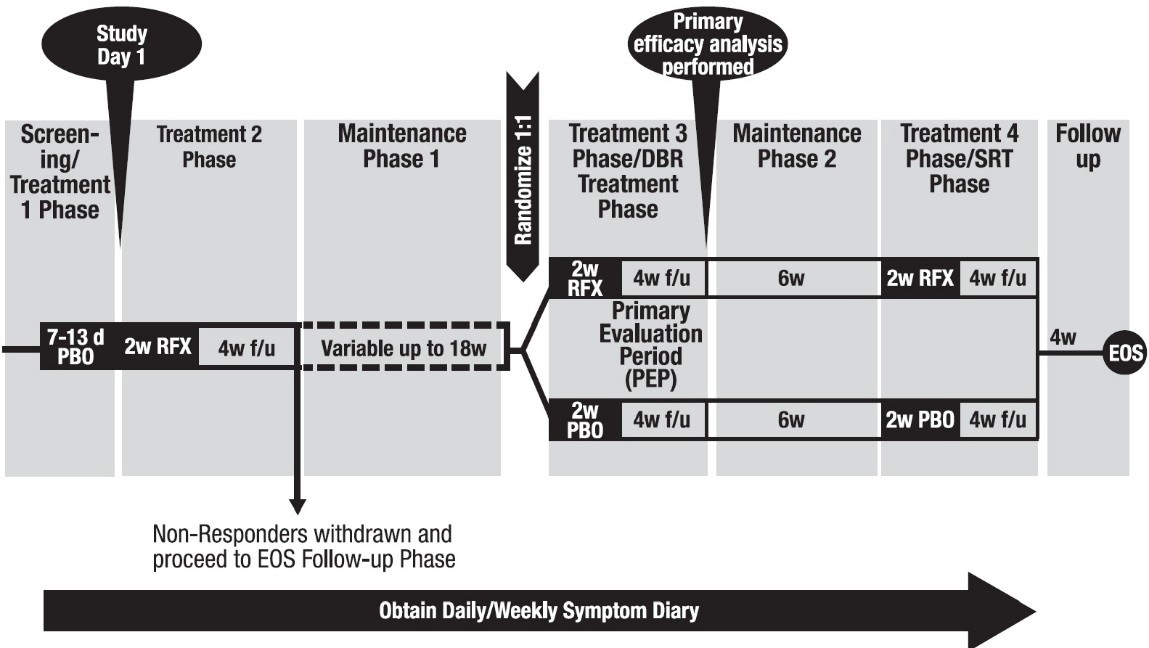 DRUG LABEL: XIFAXAN
NDC: 55154-6777 | Form: TABLET
Manufacturer: Cardinal Health 107, LLC
Category: prescription | Type: HUMAN PRESCRIPTION DRUG LABEL
Date: 20250827

ACTIVE INGREDIENTS: RIFAXIMIN 550 mg/1 1
INACTIVE INGREDIENTS: SILICON DIOXIDE; GLYCERYL PALMITOSTEARATE; MICROCRYSTALLINE CELLULOSE; POLYETHYLENE GLYCOL, UNSPECIFIED; POLYVINYL ALCOHOL, UNSPECIFIED; FERRIC OXIDE RED; SODIUM STARCH GLYCOLATE TYPE A POTATO; TALC; TITANIUM DIOXIDE

HIGHLIGHTS OF PRESCRIBING INFORMATION

These highlights do not include all the information needed to use XIFAXAN safely and effectively. See full prescribing information for XIFAXAN.
XIFAXAN ®(rifaximin) tablets, for oral use
Initial U.S. Approval: 2004
To reduce the development of drug-resistant bacteria and maintain the effectiveness of XIFAXAN and other antibacterial drugs, XIFAXAN should be used only to treat or prevent infections that are proven or strongly suspected to be caused by bacteria.

1 INDICATIONS AND USAGE

XIFAXAN is a rifamycin antibacterial indicated for:

- Treatment of travelers’ diarrhea (TD) caused by noninvasive strains of Escherichia coliin adult and pediatric patients 12 years of age and older. (1.1)
- Reduction in risk of overt hepatic encephalopathy (HE) recurrence in adults. (1.2)
- Treatment of irritable bowel syndrome with diarrhea (IBS-D) in adults. (1.3)

Limitations of Use
TD: Should not use in patients with diarrhea complicated by fever or blood in the stool or diarrhea due to pathogens other than Escherichia coli.(1.1,5.1)

2 DOSAGE AND ADMINISTRATION

Condition | Recommended Oral Dosage
TD (2.1) | 200 mg 3 times a day for 3 days
HE (2.2) | 550 mg 2 times a day
IBS-D (2.3) | 550 mg 3 times a day for 14 days. Patients who experience recurrence can be retreated up to 2 times with the same regimen.

XIFAXAN can be taken with or without food. (2.4)

3 DOSAGE FORMS AND STRENGTHS

200 mg and 550 mg tablets (3)

4 CONTRAINDICATIONS

History of hypersensitivity to rifaximin, rifamycin antimicrobial agents, or any of the components of XIFAXAN. (4))

5 WARNINGS AND PRECAUTIONS

- Travelers’ Diarrhea Not Caused by E. coli: XIFAXAN was not effective in diarrhea complicated by fever and/or blood in the stool or diarrhea due to pathogens other than E. coli. If diarrhea symptoms get worse or persist for more than 24 to 48 hours, discontinue XIFAXAN and consider alternative antibiotics. (5.1)
- Clostridium difficile-Associated Diarrhea: Evaluate if diarrhea occurs after therapy or does not improve or worsens during therapy. (5.2)
- Hepatic Impairment: Use with caution in patients with severe (Child-Pugh Class C) hepatic impairment. (5.4, 8.7)
- Concomitant P-glycoprotein (P-gp) inhibitors (e.g., cyclosporine): Caution should be exercised when concomitant use of XIFAXAN and a P-glycoprotein inhibitor is needed. (5.5,7.1)

6 ADVERSE REACTIONS

Most common adverse reactions:

- TD (≥2%): Headache (6.1)
- HE (≥10%): Peripheral edema, nausea, constipation, dizziness, fatigue, urinary tract infection, insomnia, anemia, pruritus, and ascites (6.1)
- IBS-D (≥2%): ALT increased, nausea (6.1)

To report SUSPECTED ADVERSE REACTIONS, contact Salix Pharmaceuticals at 1-800-321-4576 or FDA at 1-800-FDA-1088 or www.fda.gov/medwatch.

7 DRUG INTERACTIONS

Warfarin: Monitor INR and prothrombin time; dose adjustment of warfarin may be needed to maintain target INR range. (7.2)

8 USE IN SPECIFIC POPULATIONS

Pregnancy: May cause fetal harm (8.1)

FULL PRESCRIBING INFORMATION

1 INDICATIONS AND USAGE

To reduce the development of drug-resistant bacteria and maintain the effectiveness of XIFAXAN and other antibacterial drugs, XIFAXAN when used to treat infection should be used only to treat or prevent infections that are proven or strongly suspected to be caused by susceptible bacteria. When culture and susceptibility information are available, they should be considered in selecting or modifying antibacterial therapy. In the absence of such data, local epidemiology and susceptibility patterns may contribute to the empiric selection of therapy.

1.1 Travelers’ Diarrhea

XIFAXAN is indicated for the treatment of travelers’ diarrhea (TD) caused by noninvasive strains of Escherichia coliin adults and pediatric patients 12 years of age and older.

Limitations of Use

XIFAXAN should not be used in patients with diarrhea complicated by fever or blood in the stool or diarrhea due to pathogens other than Escherichia coli [see Warnings and Precautions (5.1), Clinical Pharmacology (12.4), Clinical Studies (14.1)].

1.2 Hepatic Encephalopathy

XIFAXAN is indicated for reduction in risk of overt hepatic encephalopathy (HE) recurrence in adults.

In the placebo-controlled trial of XIFAXAN for HE, 91% of the patients were using lactulose concomitantly. Differences in the treatment effect of those patients not using lactulose concomitantly could not be assessed.

XIFAXAN has not been studied in patients with MELD (Model for End-Stage Liver Disease) scores >25, and only 8.6% of patients in the placebo-controlled trial had MELD scores over 19. There is increased systemic exposure in patients with more severe hepatic dysfunction [see Warnings and Precautions (5.4), Use in Specific Populations (8.7), Clinical Pharmacology (12.3)].

1.3 Irritable Bowel Syndrome with Diarrhea

XIFAXAN is indicated for the treatment of irritable bowel syndrome with diarrhea (IBS-D) in adults.

2 DOSAGE AND ADMINISTRATION

2.1 Dosage for Travelers’ Diarrhea

The recommended dosage of XIFAXAN is 200 mg taken orally three times a day for 3 days.

2.2 Dosage for Hepatic Encephalopathy

The recommended dosage of XIFAXAN is 550 mg taken orally two times a day.

2.3 Dosage for Irritable Bowel Syndrome with Diarrhea

The recommended dosage of XIFAXAN is 550 mg taken orally three times a day for 14 days. Patients who experience a recurrence of symptoms can be retreated up to two times with the same dosage regimen.

2.4 Administration

XIFAXAN can be taken with or without food [see Clinical Pharmacology (12.3)].

3 DOSAGE FORMS AND STRENGTHS

XIFAXAN is a pink-colored biconvex tablet and is available in the following strengths:

- 200 mg – a round tablet debossed with “Sx” on one side and plain on the other.
- 550 mg – an oval tablet debossed with “rfx” on one side and plain on the other.

4 CONTRAINDICATIONS

XIFAXAN is contraindicated in patients with a hypersensitivity to rifaximin, any of the rifamycin antimicrobial agents, or any of the components in XIFAXAN. Hypersensitivity reactions have included exfoliative dermatitis, angioneurotic edema, and anaphylaxis [see Adverse Reactions (6.2)] .

5 WARNINGS AND PRECAUTIONS

5.1 Travelers’ Diarrhea Not Caused by Escherichia coli

XIFAXAN was not found to be effective in patients with diarrhea complicated by fever and/or blood in the stool or diarrhea due to pathogens other than Escherichia coli.

Discontinue XIFAXAN if diarrhea symptoms get worse or persist more than 24 to 48 hours and alternative antibiotic therapy should be considered.

XIFAXAN is not effective in cases of travelers’ diarrhea due to Campylobacter jejuni. The effectiveness of XIFAXAN in travelers’ diarrhea caused by Shigellaspp. and Salmonellaspp. has not been proven. XIFAXAN should not be used in patients where Campylobacter jejuni, Shigellaspp., or Salmonellaspp. may be suspected as causative pathogens [ see Indications and Usage (1.1)].

5.2 Clostridium difficile-Associated Diarrhea

Clostridium difficile-associated diarrhea (CDAD) has been reported with use of nearly all antibacterial agents, including XIFAXAN, and may range in severity from mild diarrhea to fatal colitis. Treatment with antibacterial agents alters the normal flora of the colon which may lead to overgrowth of C. difficile.

C. difficileproduces toxins A and B which contribute to the development of CDAD. Hypertoxin producing strains of C. difficilecause increased morbidity and mortality, as these infections can be refractory to antimicrobial therapy and may require colectomy. CDAD must be considered in all patients who present with diarrhea following antibiotic use. Careful medical history is necessary since CDAD has been reported to occur over two months after the administration of antibacterial agents.

If CDAD is suspected or confirmed, ongoing antibiotic use not directed against C. difficilemay need to be discontinued. Appropriate fluid and electrolyte management, protein supplementation, antibiotic treatment of C . difficile,and surgical evaluation should be instituted as clinically indicated.

5.3 Development of Drug-Resistant Bacteria

Prescribing XIFAXAN for travelers’ diarrhea in the absence of a proven or strongly suspected bacterial infection or a prophylactic indication is unlikely to provide benefit to the patient and increases the risk of the development of drug-resistant bacteria.

5.4 Severe (Child-Pugh Class C) Hepatic Impairment

There is increased systemic exposure in patients with severe hepatic impairment. The clinical trials were limited to patients with MELD scores <25. Therefore, caution should be exercised when administering XIFAXAN to patients with severe hepatic impairment (Child-Pugh Class C) [ see Use in Specific Populations (8.7), Clinical Studies (14.2)].

5.5 Concomitant Use with P-glycoprotein Inhibitors

Concomitant administration of drugs that are P-glycoprotein (P-gp) inhibitors with XIFAXAN can substantially increase the systemic exposure to rifaximin. Caution should be exercised when concomitant use of XIFAXAN and a P-gp inhibitor such as cyclosporine is needed. In patients with hepatic impairment, a potential additive effect of reduced metabolism and concomitant P-gp inhibitors may further increase the systemic exposure to rifaximin [see Drug Interactions (7.1), Clinical Pharmacology (12.3)].

6 ADVERSE REACTIONS

The following clinically significant adverse reactions are described elsewhere in labeling:

- Clostridium difficile-associated diarrhea [see Warnings and Precautions (5.2)]

6.1 Clinical Trials Experience

Because clinical trials are conducted under widely varying conditions, adverse reaction rates observed in the clinical trials of a drug cannot be directly compared to rates in the clinical trials of another drug and may not reflect the rates observed in practice.

Travelers’ Diarrhea

The safety of XIFAXAN 200 mg taken three times a day was evaluated in patients with travelers’ diarrhea consisting of 320 patients in two placebo-controlled clinical trials with 95% of patients receiving three or four days of treatment with XIFAXAN. The population studied had a mean age of 31.3 (18-79) years of which approximately 3% were ≥65 years old, 53% were male and 84% were White, 11% were Hispanic.

Discontinuations due to adverse reactions occurred in 0.4% of patients. The adverse reactions leading to discontinuation were taste loss, dysentery, weight decrease, anorexia, nausea and nasal passage irritation.

The adverse reaction that occurred at a frequency ≥2% in XIFAXAN-treated patients (n=320) at a higher rate than placebo (n=228) in the two placebo-controlled trials of TD was:

- headache (10% XIFAXAN, 9% placebo)

Hepatic Encephalopathy
Trial 1
The data described in Table 1 reflect exposure to XIFAXAN in 348 patients, including 265 exposed for 6 months and 202 exposed for more than a year (mean exposure was 364 days). The safety of XIFAXAN 550 mg taken two times a day for reducing the risk of overt HE recurrence in adult patients was evaluated in a 6-month placebo-controlled clinical trial (n=140) and in a long-term follow-up study (n=280) [see Clinical Studies (14.2)] . The population studied had a mean age of 56 (range: 21 to 82) years; approximately 20% of the patients were ≥65 years old, 61% were male, 86% were White, and 4% were Black. Ninety-one percent of patients in the trial were taking lactulose concomitantly. The most common adverse reactions that occurred at an incidence ≥5% and at a higher incidence in XIFAXAN-treated subjects than in the placebo group in the 6-month trial are provided in Table 1.

Table 1: Common Adverse Reactions*from a Clinical Study of XIFAXAN in Adult Patients with Hepatic Encephalopathy (Trial 1)

Adverse Reaction | XIFAXAN Tablets; 550 mg TWICE DAILY; (N=140) n (%) | Placebo; (N=159) n (%)
Peripheral edema | 21 (15%) | 13 (8%)
Nausea | 20 (14%) | 21 (13%)
Dizziness | 18 (13%) | 13 (8%)
Fatigue | 17 (12%) | 18 (11%)
Ascites | 16 (11%) | 15 (9%)
Muscle spasms | 13 (9%) | 11 (7%)
Pruritus | 13 (9%) | 10 (6%)
Abdominal pain | 12 (9%) | 13 (8%)
Anemia | 11 (8%) | 6 (4%)
Depression | 10 (7%) | 8 (5%)
Nasopharyngitis | 10 (7%) | 10 (6%)
Abdominal pain upper | 9 (6%) | 8 (5%)
Arthralgia | 9 (6%) | 4 (3%)
Dyspnea | 9 (6%) | 7 (4%)
Pyrexia | 9 (6%) | 5 (3%)
Rash | 7 (5%) | 1. (4%)

*Adverse reactions that occurred in ≥5% of XIFAXAN-treated patients and greater than in patients who received placebo

Trial 2
The data described in Table 2 reflect exposure to XIFAXAN in 221 of 222 randomized subjects, exposed for a median duration of 169 days, with 113 exposed to XIFAXAN monotherapy and 108 exposed to XIFAXAN added onto lactulose in a six-month active-controlled trial [see Clinical Studies (14.2)]. The population studied had a mean age of 58; approximately 63% of subjects were male. The most common adverse reactions that occurred at an incidence ≥5% are provided in Table 2.

Table 2: Common Adverse Reactions*from a Clinical Study of XIFAXAN + Lactulose Compared to XIFAXAN Monotherapy in Adult Patients with Hepatic Encephalopathy (Trial 2)

Adverse Reaction | XIFAXAN Tablets 550 mg TWICE DAILY + Lactulose (N=108) n (%) | XIFAXAN Tablets 550 mg TWICE DAILY (N=113) n (%)
Peripheral edema | 15 (14%) | 19 (17%)
Insomnia | 15 (14%) | 13 (12%)
Ascites | 14 (13%) | 8 (7%)
Diarrhea | 13 (12%) | 6 (5%)
Nausea | 11 (10%) | 17 (15%)
Muscle spasms | 11 (10%) | 9 (8%)
Dyspnea | 10 (9%) | 8 (7%)
Anxiety | 10 (9%) | 6 (5%)
Constipation | 9 (8%) | 18 (16%)
Fatigue | 9 (8%) | 16 (14%)
Urinary tract infection | 9 (8%) | 13 (12%)
Abdominal pain | 8 (7%) | 8 (7%)
Pruritus | 6 (6%) | 11 (10%)
Decreased appetite | 5 (5%) | 8 (7%)
Headache | 5 (5%) | 8 (7%)
Cough | 5 (5%) | 6 (6%)
Renal failure acute | 5 (5%) | 7 (6%)
Vomiting | 6 (5%) | 6 (6%)
Anemia | 3 (3%) | 11 (10%)

* Adverse reactions that occurred in ≥5% of patients receiving XIFAXAN in either treatment group

Irritable Bowel Syndrome with Diarrhea

The safety of XIFAXAN for the treatment of IBS-D was evaluated in 3 placebo-controlled studies in which 952 patients were randomized to XIFAXAN 550 mg three times a day for 14 days. Across the 3 studies, 96% of patients received at least 14 days of treatment with XIFAXAN. In Trials 1 and 2, 624 patients received only one 14-day treatment. Trial 3 evaluated the safety of XIFAXAN in 328 patients who received 1 open-label treatment and 2 double-blind repeat treatments of 14 days each over a period of up to 46 weeks. The combined population studied had a mean age of 47 (range: 18 to 88) years of whom approximately 11% of the patients were ≥65 years old, 72% were female, 88% were White, 9% were Black, and 12% were Hispanic.

The adverse reaction that occurred at a frequency ≥2% in XIFAXAN-treated patients at a higher rate than placebo in Trials 1 and 2 for IBS-D was:

- nausea (3% XIFAXAN, 2% placebo)

The adverse reactions that occurred at a frequency ≥2% in XIFAXAN-treated patients (n=328) at a higher rate than placebo (n=308) in Trial 3 for IBS-D during the double-blind treatment phase were:

- ALT increased (XIFAXAN 2%, placebo 1%)
- nausea (XIFAXAN 2%, placebo 1%)

Less Common Adverse Reactions
The following adverse reactions, presented by body system, were reported in less than 2% of patients in clinical trials of TD and IBS-D and in less than 5% of patients in clinical trials of HE:

Hepatobiliary disorders:Clostridium colitis

Investigations:Increased blood creatine phosphokinase

Musculoskeletal and connective tissue disorders:Myalgia

6.2 Postmarketing Experience

The following adverse reactions have been identified during post-approval use of XIFAXAN. Because these reactions are reported voluntarily from a population of unknown size, estimates of frequency cannot be made. These reactions have been chosen for inclusion due to either their seriousness, frequency of reporting, or causal connection to XIFAXAN.

Infections and Infestations

Cases of C. difficile-associated colitis have been reported [see Warnings and Precautions (5.2)].

Hypersensitivity Reactions

Exfoliative dermatitis, rash, angioneurotic edema (swelling of face and tongue and difficulty swallowing), urticaria, flushing, pruritus and anaphylaxis have been reported. These events occurred as early as within 15 minutes of drug administration.

Musculoskeletal and Connective Tissue Disorders

Cases of rhabdomyolysis have been reported in patients with cirrhosis, with and without concomitant statin use.

Severe Cutaneous Adverse Reactions

Severe cutaneous adverse reactions, including Stevens-Johnson syndrome (SJS) and toxic epidermal necrolysis (TEN), have been reported in association with the use of rifaximin in patients with cirrhosis. Discontinue rifaximin at the first signs or symptoms of severe cutaneous adverse reactions or other signs of hypersensitivity and conduct a clinical evaluation.

7 DRUG INTERACTIONS

7.1 P-glycoprotein Inhibitors

Concomitant administration of cyclosporine, an inhibitor of P-gp and OATPs significantly increased the systemic exposure of rifaximin. In patients with hepatic impairment, a potential additive effect of reduced metabolism and concomitant P-gp inhibitors may further increase the systemic exposure to rifaximin. Caution should be exercised when concomitant use of XIFAXAN and a P-gp inhibitor such as cyclosporine is needed [see Warnings and Precautions (5.5), Clinical Pharmacology (12.3)].

7.2 Warfarin

Changes in INR have been reported postmarketing in patients receiving rifaximin and warfarin concomitantly. Monitor INR and prothrombin time. Dose adjustment of warfarin may be needed to maintain target INR range. See prescribing information for warfarin.

7.3 CYP3A4 Substrates

An in vitrostudy has suggested that rifaximin induces CYP3A4 [see Clinical Pharmacology (12.3)] . However, in patients with normal liver function, XIFAXAN at the recommended dosing regimen is not expected to induce CYP3A4. It is unknown whether rifaximin can have a significant effect on the pharmacokinetics of concomitant CYP3A4 substrates in patients with reduced liver function who have elevated rifaximin concentrations.

8 USE IN SPECIFIC POPULATIONS

8.1 Pregnancy

Risk Summary

There are no available data on XIFAXAN use in pregnant women to inform any drug-associated risks. Teratogenic effects were observed in animal reproduction studies following administration of rifaximin to pregnant rats and rabbits during organogenesis at doses approximately 0.9 to 5 times and 0.7 to 33 times, respectively of the recommended human doses of 600 mg to 1,650 mg per day. In rabbits, ocular, oral and maxillofacial, cardiac, and lumbar spine malformations were observed. Ocular malformations were observed in both rats and rabbits at doses that caused reduced maternal body weight gain [see Data]. In the U.S. general population, the estimated background risk of major birth defects and miscarriage in clinically recognized pregnancies is 2 to 4% and 15 to 20%, respectively. Advise pregnant women of the potential risk to a fetus.

Data

Animal Data

Rifaximin was teratogenic in rats at doses of 150 to 300 mg/kg (approximately 2.5 to 5 times the recommended dose for TD [600 mg per day], and approximately 1.3 to 2.6 times the recommended dose for HE [1,100 mg per day], and approximately 0.9 to 1.8 times the recommended dose for IBS-D [1,650 mg per day] adjusted for body surface area). Rifaximin was teratogenic in rabbits at doses of 62.5 to 1,000 mg/kg (approximately 2 to 33 times the recommended dose for TD [600 mg per day], and approximately 1.1 to 18 times the recommended dose for HE [1,100 mg per day], and approximately 0.7 to 12 times the recommended dose for IBS-D [1,650 mg per day] adjusted for body surface area). These effects include cleft palate, agnathia, jaw shortening, hemorrhage, eye partially open, small eyes, brachygnathia, incomplete ossification, and increased thoracolumbar vertebrae.

A pre and postnatal development study in rats showed no evidence of any adverse effect on pre and postnatal development at oral doses of rifaximin up to 300 mg/kg per day (approximately 5 times the recommended dose for TD [600 mg per day], and approximately 2.6 times the recommended dose for HE [1,100 mg per day], and approximately 1.8 times the recommended dose for IBS-D [1,650 mg per day] adjusted for body surface area).

8.2 Lactation

Risk Summary

There is no information regarding the presence of rifaximin in human milk, the effects of rifaximin on the breastfed infant, or the effects of rifaximin on milk production. The development and health benefits of breastfeeding should be considered along with the mother’s clinical need for XIFAXAN and any potential adverse effects on the breastfed infant from XIFAXAN or from the underlying maternal condition.

8.4 Pediatric Use

The safety and effectiveness of XIFAXAN has not been established in pediatric patients less than 12 years of age with TD or in patients less than 18 years of age for HE and IBS-D.

8.5 Geriatric Use

Of the total number of patients in the clinical study of XIFAXAN for HE, 19% of patients were 65 and over, while 2% were 75 and over. In the clinical studies of IBS-D, 11% of patients were 65 and over, while 2% were 75 and over. No overall differences in safety or effectiveness were observed between these subjects and younger subjects for either indication. Clinical studies with XIFAXAN for TD did not include sufficient numbers of patients aged 65 and over to determine whether they respond differently than younger subjects. Other reported clinical experience has not identified differences in responses between the elderly and younger patients, but greater sensitivity of some older individuals cannot be ruled out.

8.6 Renal Impairment

The pharmacokinetics of rifaximin in patients with impaired renal function has not been studied.

8.7 Hepatic Impairment

Following administration of XIFAXAN 550 mg twice daily to patients with a history of hepatic encephalopathy, the systemic exposure (i.e., AUC τ) of rifaximin was about 10-, 14-, and 21-fold higher in those patients with mild (Child-Pugh Class A), moderate (Child-Pugh Class B) and severe (Child-Pugh Class C) hepatic impairment, respectively, compared to that in healthy volunteers. No dosage adjustment is recommended because rifaximin is presumably acting locally. Nonetheless, caution should be exercised when XIFAXAN is administered to patients with severe hepatic impairment [see Warnings and Precautions (5.4), Clinical Pharmacology (12.3), Clinical Studies (14.2)] .

10 OVERDOSAGE

No specific information is available on the treatment of overdosage with XIFAXAN. In clinical studies at doses higher than the recommended dose (greater than 600 mg per day for TD, greater than 1,100 mg per day for HE or greater than 1,650 mg per day for IBS-D), adverse reactions were similar in subjects who received doses higher than the recommended dose and placebo. In the case of overdosage, discontinue XIFAXAN, treat symptomatically, and institute supportive measures as required.

11 DESCRIPTION

XIFAXAN tablets contain rifaximin, a non-aminoglycoside semi-synthetic, nonsystemic antibiotic derived from rifamycin SV. Rifaximin is a structural analog of rifampin. The chemical name for rifaximin is (2 S,16 Z,18 E,20 S,21 S,22 R,23 R,24 R,25 S,26 S,27 S,28 E)-5,6,21,23,25-pentahydroxy-27-methoxy-2,4,11,16,20,22,24,26-octamethyl-2,7-(epoxypentadeca-[1,11,13]trienimino)benzofuro[4,5-e]pyrido[1,2-á]-benzimidazole-1,15(2 H)-dione,25- acetate. The empirical formula is C43H51N3O11 and its molecular weight is 785.9. The chemical structure is represented below:

XIFAXAN tablets for oral administration are film-coated and contain 200 mg or 550 mg of rifaximin.

Inactive ingredients:

Each 200 mg tablet contains colloidal silicon dioxide, disodium edetate, glycerol palmitostearate, hypromellose, microcrystalline cellulose, propylene glycol, red iron oxide, sodium starch glycolate, talc, and titanium dioxide.

Each 550 mg tablet contains colloidal silicon dioxide, glycerol palmitostearate, microcrystalline cellulose, polyethylene glycol/macrogol, polyvinyl alcohol, red iron oxide, sodium starch glycolate, talc, and titanium dioxide.

12 CLINICAL PHARMACOLOGY

12.1 Mechanism of Action

Rifaximin is an antibacterial drug [see Clinical Pharmacology (12.4)].

12.3 Pharmacokinetics

Absorption

In healthy subjects, the mean time to reach peak rifaximin plasma concentrations was about an hour and the mean Cmax ranged 2.4 to 4 ng/mL after a single dose and multiple doses of XIFAXAN 550 mg.

Travelers’ Diarrhea

Systemic absorption of XIFAXAN (200 mg three times daily) was evaluated in 13 subjects challenged with shigellosis on Days 1 and 3 of a three-day course of treatment. Rifaximin plasma concentrations and exposures were low and variable. There was no evidence of accumulation of rifaximin following repeated administration for 3 days (9 doses). Peak plasma rifaximin concentrations after 3 and 9 consecutive doses ranged from 0.81 to 3.4 ng/mL on Day 1 and 0.68 to 2.26 ng/mL on Day 3. Similarly, AUC0-last estimates were 6.95 ± 5.15 ng•h/mL on Day 1 and 7.83 ± 4.94 ng•h/mL on Day 3.

XIFAXAN is not suitable for treating systemic bacterial infections because of limited systemic exposure after oral administration [see Warnings and Precautions (5.1)] .

Hepatic Encephalopathy

Mean rifaximin exposure (AUCτ) in patients with a history of HE was approximately 12-fold higher than that observed in healthy subjects. Among patients with a history of HE, the mean AUC in patients with Child-Pugh Class C hepatic impairment was 2-fold higher than in patients with Child-Pugh Class A hepatic impairment [see Warnings and Precautions (5.4), Use in Specific Populations (8.7)].

Irritable Bowel Syndrome with Diarrhea

In patients with irritable bowel syndrome with diarrhea (IBS-D) treated with XIFAXAN 550 mg three times a day for 14 days, the median Tmax was 1 hour and mean Cmax and AUC were generally comparable with those in healthy subjects. After multiple doses, AUCtau was 1.65-fold higher than that on Day 1 in IBS-D patients (see Table 3).

Table 1. Mean (± SD) Pharmacokinetic Parameters of Rifaximin Following XIFAXAN 550 mg Three Times a Day in IBS-D Patients and Healthy Subjects
 | Healthy Subjects |  | IBS-D Patients
 | Single- Dose (Day 1) n=12 | Multiple- Dose (Day 14) n=14 | Single- Dose (Day 1) n=24 | Multiple- Dose (Day 14) n=24
C max (ng/mL) | 4.04 (1.51) | 2.39 (1.28) | 3.49 (1.36) | 4.22 (2.66)
T max (h)ª | 0.75 (0.5-2.1) | 1.00 (0.5-2.0) | 0.78 (0-2) | 1.00 (0.5-2)
AUC tau (ng•h/mL) | 10.4 (3.47) | 9.30 (2.7) | 9.69 (4.16) | 16.0 (9.59)
Half-life (h) | 1.83 (1.38) | 5.63 (5.27) | 3.14 (1.71) | 6.08 (1.68)

ª Median (range)

Food Effect in Healthy Subjects

A high-fat meal consumed 30 minutes prior to XIFAXAN dosing in healthy subjects delayed the mean time to peak plasma concentration from 0.75 to 1.5 hours and increased the systemic exposure (AUC) of rifaximin by 2-fold but did not significantly affect C max.

Dose-Proportionality

After oral administration of XIFAXAN 200 mg, 400 mg, or 600 mg, rifaximin systemic exposures increased dose- dependently by approximately 2-fold for both AUClast and Cmax from 200 mg to 400 mg, but with a less than dose- proportional increase of 1.3-fold for both AUClast and Cmax from 400 mg to 600 mg administration.

Distribution

Rifaximin is moderately bound to human plasma proteins. In vivo, the mean protein binding ratio was 67.5% in healthy subjects and 62% in patients with hepatic impairment when XIFAXAN was administered.

Elimination

The mean half-life of rifaximin in healthy subjects at steady-state was 5.6 hours and was 6 hours in IBS-D patients.

Metabolism

In an in vitrostudy, rifaximin was metabolized mainly by CYP3A4. Rifaximin accounted for 18% of radioactivity in plasma suggesting that the absorbed rifaximin undergoes extensive metabolism.

Excretion

In a mass balance study, after administration of 400 mg ^14C-rifaximin orally to healthy volunteers, of the 96.94% total recovery, 96.62% of the administered radioactivity was recovered in feces mostly as the unchanged drug and 0.32% was recovered in urine mostly as metabolites with 0.03% as the unchanged drug.

Biliary excretion of rifaximin was suggested by a separate study in which rifaximin was detected in the bile after cholecystectomy in patients with intact gastrointestinal mucosa.

Specific Populations

Hepatic Impairment

The systemic exposure of rifaximin was markedly elevated in patients with hepatic impairment compared to healthy subjects.

The pharmacokinetics of rifaximin in patients with a history of HE was evaluated after administration of XIFAXAN 550 mg twice a day. The pharmacokinetic parameters were associated with a high variability and mean rifaximin exposure (AUC τ) in patients with a history of HE was higher compared to those in healthy subjects. The mean AUC τin patients with hepatic impairment of Child-Pugh Class A, B, and C was 10-, 14-, and 21-fold higher, respectively, compared to that in healthy subjects (see Table 4).

Table 2. Mean (± SD) Pharmacokinetic Parameters of Rifaximin at Steady-State in Patients with a History of Hepatic Encephalopathy by Child-Pugh Class [Cross-study comparison with pharmacokinetic parameters in healthy subjects]
 | Healthy Subjects (n=14) | Child-Pugh Class
 | Healthy Subjects (n=14) | A (n=18) | B (n=15) | C (n=6)
AUC tau (ng•h/mL) | 12.3 ± 4.8 | 118 ± 67.8 | 169 ± 55.7 | 257 ± 100.2
C max (ng/mL) | 3.4 ± 1.6 | 19.5 ± 11.4 | 25.4 ± 11.9 | 39.7 ± 13.4
T max (h) | 0.8 (0.5, 4.0) | 1 (0.9, 10) | 1 (1.0, 4.2) | - 1 (0, 2)

Renal Impairment

The pharmacokinetics of rifaximin in patients with impaired renal function has not been studied.

Drug Interaction Studies

An in vitrostudy suggests that rifaximin is a substrate of CYP3A4.

In vitrorifaximin is a substrate of P-glycoprotein, OATP1A2, OATP1B1, and OATP1B3. Rifaximin is not a substrate of OATP2B1.

Cyclosporine

In vitroin the presence of P-glycoprotein inhibitor, verapamil, the efflux ratio of rifaximin was reduced greater than 50%. In a clinical drug interaction study, mean Cmax for rifaximin was increased 83-fold, from 0.48 to 40.0 ng/mL; mean AUC∞ was increased 124-fold, from 2.54 to 314 ng●h/mL following co-administration of a single dose of XIFAXAN 550 mg with a single 600 mg dose of cyclosporine, an inhibitor of P-glycoprotein [see Drug Interactions (7.1)] .

Cyclosporine is also an inhibitor of OATP, breast cancer resistance protein (BCRP) and a weak inhibitor of CYP3A4. The relative contribution of inhibition of each transporter by cyclosporine to the increase in rifaximin exposure is unknown.

Effect of rifaximin on other drugs

In in vitrodrug interaction studies, the IC 50values for rifaximin was >50 micromolar (~60 mcg) for CYP isoforms 1A2, 2A6, 2B6, 2C9, 2C19, 2D6, and 2E1. In vitroIC 50value of rifaximin for CYP3A4 was 25 micromolar. Based on in vitrostudies, clinically significant drug interaction via inhibition of 1A2, 2A6, 2B6, 2C9, 2C19, 2D6, 2E1 and 3A4 by rifaximin is not expected.

The inhibitory effect of rifaximin on P-glycoprotein transport was observed in an in vitrostudy. The effect of rifaximin on P-gp transporter was not evaluated in vivo.

In in vitrostudies, rifaximin at 3 micromolar inhibited the uptake of estradiol glucuronide via OATP1B1 by 64% and via OATP1B3 by 70% while the uptake of estrone sulfate via OATP1A2 was inhibited by 40%. The inhibitory potential of rifaximin on these transporters at the clinically relevant concentrations is unknown.

Midazolam

In an in vitrostudy, rifaximin was shown to induce CYP3A4 at the concentration of 0.2 micromolar. No significant induction of CYP3A4 enzyme using midazolam as a substrate was observed when rifaximin was administered three times a day for 7 days at 200 mg and 550 mg doses in two clinical drug interaction studies in healthy subjects.

The effect of XIFAXAN 200 mg administered orally every 8 hours for 3 days and for 7 days on the pharmacokinetics of a single dose of either 2 mg intravenous midazolam or 6 mg oral midazolam was evaluated in healthy subjects. No significant difference was observed in the systemic exposure or elimination of intravenous or oral midazolam or its major metabolite, 1’-hydroxymidazolam, between midazolam alone or together with XIFAXAN. Therefore, XIFAXAN was not shown to significantly affect intestinal or hepatic CYP3A4 activity for the 200 mg three times a day dosing regimen.

When a single dose of 2 mg midazolam was orally administered after administration of XIFAXAN 550 mg three times a day for 7 days and 14 days to healthy subjects, the mean AUC of midazolam was 3.8% and 8.8% lower, respectively, than when midazolam was administered alone. The mean C maxof midazolam was lower by 4 to 5% when XIFAXAN was administered for 7-14 days prior to midazolam administration. This degree of interaction is not considered clinically meaningful.

Oral Contraceptives Containing Ethinyl Estradiol and Norgestimate

The oral contraceptive study utilized an open-label, crossover design in 28 healthy female subjects to determine if XIFAXAN 200 mg orally administered three times a day for 3 days (the dosing regimen for travelers’ diarrhea) altered the pharmacokinetics of a single dose of an oral contraceptive containing 0.07 mg ethinyl estradiol and 0.5 mg norgestimate. Results showed that the pharmacokinetics of single doses of ethinyl estradiol and norgestimate were not altered by XIFAXAN.

An open-label oral contraceptive study was conducted in 39 healthy female subjects to determine if XIFAXAN 550 mg orally administered three times a day for 7 days altered the pharmacokinetics of a single dose of an oral contraceptive containing 0.025 mg of ethinyl estradiol (EE) and 0.25 mg norgestimate (NGM). Mean C maxof EE and NGM was lower by 25% and 13%, after the 7-day XIFAXAN regimen than when the oral contraceptive was given alone. The mean AUC values of NGM active metabolites were lower by 7% to approximately 11%, while AUC of EE was not altered in presence of rifaximin. The clinical relevance of the C maxand AUC reductions in the presence of rifaximin is not known.

12.4 Microbiology

Mechanism of Action

Rifaximin is a semi-synthetic derivative of rifampin and acts by binding to the beta-subunit of bacterial DNA-dependent RNA polymerase blocking one of the steps in transcription. This results in inhibition of bacterial protein synthesis and consequently inhibits the growth of bacteria.

Resistance

Resistance to rifaximin is caused primarily by mutations in the rpoBgene. This changes the binding site on DNA dependent RNA polymerase and decreases rifaximin binding affinity, thereby reducing efficacy. Cross-resistance between rifaximin and other classes of antimicrobials has not been observed.

Antibacterial Activity

Rifaximin has been shown to be active against most isolates of the following microorganisms, both in vitroand in clinical infections [see Indications and Usage (1.1)]:

1. Aerobic bacteria
2. Gram-negative bacteria
3. Escherichia coli(enterotoxigenic and enteroaggregative strains)

Susceptibility Testing

For specific information regarding susceptibility test interpretive criteria, and associated test methods and quality control standards recognized by FDA for this drug, please see https://www.fda.gov/STIC.

13 NONCLINICAL TOXICOLOGY

13.1 Carcinogenesis, Mutagenesis, Impairment of Fertility

Malignant schwannomas in the heart were significantly increased in male Crl: CD (SD) rats that received rifaximin by oral gavage for two years at 150 to 250 mg/kg per day (doses equivalent to 2.4 to 4 times the recommended dose of 200 mg three times daily for TD, and equivalent to 1.3 to 2.2 times the recommended dose of 550 mg twice daily for HE, based on relative body surface area comparisons). There was no increase in tumors in Tg.rasH2 mice dosed orally with rifaximin for 26 weeks at 150 to 2,000 mg/kg per day (doses equivalent to 1.2 to 16 times the recommended daily dose for TD and equivalent to 0.7 to 9 times the recommended daily dose for HE, based on relative body surface area comparisons).

Rifaximin was not genotoxic in the bacterial reverse mutation assay, chromosomal aberration assay, rat bone marrow micronucleus assay, rat hepatocyte unscheduled DNA synthesis assay, or the CHO/HGPRT mutation assay. There was no effect on fertility in male or female rats following the administration of rifaximin at doses up to 300 mg/kg (approximately 5 times the clinical dose of 600 mg per day for TD, and approximately 2.6 times the clinical dose of 1,100 mg per day for HE, adjusted for body surface area).

14 CLINICAL STUDIES

14.1 Travelers’ Diarrhea

The efficacy of XIFAXAN given as 200 mg orally taken three times a day for 3 days was evaluated in 2 randomized, multi‑center, double-blind, placebo-controlled studies in adult subjects with travelers’ diarrhea. One study was conducted at clinical sites in Mexico, Guatemala, and Kenya (Study 1). The other study was conducted in Mexico, Guatemala, Peru, and India (Study 2). Stool specimens were collected before treatment and 1 to 3 days following the end of treatment to identify enteric pathogens. The predominant pathogen in both studies was Escherichia coli.

The clinical efficacy of XIFAXAN was assessed by the time to return to normal, formed stools, and resolution of symptoms. The primary efficacy endpoint was time to last unformed stool (TLUS) which was defined as the time to the last unformed stool passed, after which clinical cure was declared. Table 5 displays the median TLUS and the number of patients who achieved clinical cure for the intent to treat (ITT) population of Study 1. The duration of diarrhea was significantly shorter in patients treated with XIFAXAN than in the placebo group. More patients treated with XIFAXAN were classified as clinical cures than were those in the placebo group.

Table 3. Clinical Response in Study 1 (ITT population)
 | XIFAXAN (n=125) | Placebo (n=129) | Estimate (97.5% CI)
Median TLUS (hours) | 32.5 | 58.6 | 2 [Hazard Ratio (p-value <0.001)] (1.26, 2.50)
Clinical cure, n (%) | 99 (79) | 78 (60) | 19 [Difference in rates (p-value <0.01)] (5.3, 32.1)

Microbiological eradication (defined as the absence of a baseline pathogen in culture of stool after 72 hours of therapy) rates for Study 1 are presented in Table 6 for patients with any pathogen at baseline and for the subset of patients with Escherichia coliat baseline. Escherichia coliwas the only pathogen with sufficient numbers to allow comparisons between treatment groups.

Even though XIFAXAN had microbiologic activity similar to placebo, it demonstrated a clinically significant reduction in duration of diarrhea and a higher clinical cure rate than placebo. Therefore, patients should be managed based on clinical response to therapy rather than microbiologic response.

Table 4. Microbiologic Eradication Rates in Study 1 Subjects with a Baseline Pathogen
 | XIFAXAN | Placebo
Overall | 48/70 (69) | 41/61; (67)
E. coli | 38/53; (72) | 40/54; (74)

The results of Study 2 supported the results presented for Study 1. In addition, this study provided evidence that subjects treated with XIFAXAN with fever and/or blood in the stool at baseline had prolonged TLUS. These subjects had lower clinical cure rates than those without fever or blood in the stool at baseline. Many of the patients with fever and/or blood in the stool (dysentery-like diarrheal syndromes) had invasive pathogens, primarily Campylobacter jejuni, isolated in the baseline stool.

Also in this study, the majority of the subjects treated with XIFAXAN who had Campylobacter jejuniisolated as a sole pathogen at baseline failed treatment and the resulting clinical cure rate for these patients was 23.5% (4/17). In addition to not being different from placebo, the microbiologic eradication rates for subjects with Campylobacter jejuniisolated at baseline were much lower than the eradication rates seen for Escherichia coli.

In an unrelated open-label, pharmacokinetic study of oral XIFAXAN 200 mg taken every 8 hours for 3 days, 15 adult subjects were challenged with Shigella flexneri2a, of whom 13 developed diarrhea or dysentery and were treated with XIFAXAN. Although this open-label challenge trial was not adequate to assess the effectiveness of XIFAXAN in the treatment of shigellosis, the following observations were noted: eight subjects received rescue treatment with ciprofloxacin either because of lack of response to XIFAXAN treatment within 24 hours (2), or because they developed severe dysentery (5), or because of recurrence of Shigella flexneri2a in the stool (1); five of the 13 subjects received ciprofloxacin although they did not have evidence of severe disease or relapse.

14.2 Hepatic Encephalopathy

Trial 1
The efficacy of XIFAXAN 550 mg taken orally two times a day was evaluated in a randomized, placebo-controlled, double-blind, multi-center 6-month trial of adult subjects from the U.S., Canada, and Russia who were defined as being in remission (Conn score of 0 or 1) from hepatic encephalopathy (HE). Eligible subjects had ≥2 episodes of HE associated with chronic liver disease in the previous 6 months.

A total of 299 subjects were randomized to receive either XIFAXAN (N=140) or placebo (N=159) in this study. Patients had a mean age of 56 years (range, 21-82 years), 81% <65 years of age, 61% were male, and 86% were White. At baseline, 67% of patients had a Conn score of 0 and 68% had an asterixis grade of 0. Patients had MELD scores of either ≤10 (27%) or 11 to 18 (64%) at baseline. No patients were enrolled with a MELD score of >25. Nine percent of the patients were Child-Pugh Class C. Lactulose was concomitantly used by 91% of the patients in each treatment arm of the study. Per the study protocol, patients were withdrawn from the study after experiencing a breakthrough HE episode. Other reasons for early study discontinuation included: adverse reactions (XIFAXAN 6%; placebo 4%), patient request to withdraw (XIFAXAN 4%; placebo 6%), and other (XIFAXAN 7%; placebo 5%).

The primary endpoint was the time to first breakthrough overt HE episode. A breakthrough overt HE episode was defined as a marked deterioration in neurological function and an increase of Conn score to Grade ≥2. In patients with a baseline Conn score of 0, a breakthrough overt HE episode could also be defined as an increase in Conn score of 1 and asterixis grade of 1.

Breakthrough overt HE episodes were experienced by 31 of 140 subjects (22%) in the XIFAXAN group and by 73 of 159 subjects (46%) in the placebo group during the 6-month treatment period. Comparison of Kaplan-Meier estimates of event-free curves showed XIFAXAN significantly reduced the risk of HE breakthrough by 58% during the 6-month treatment period. Presented below in Figure 1 is the Kaplan-Meier event-free curve for all subjects (n=299) in the study.

Figure 1: Kaplan-Meier Event-Free Curves ^1in HE Study (Time to First Breakthrough-HE Episode up to 6 Months of Treatment, Day 170) (ITT Population) ^2

1. Note: Open diamonds and open triangles represent censored subjects.
  ¹Event-free refers to non-occurrence of breakthrough HE
  ²91% of subjects were taking concomitant lactulose

When the results were evaluated by the following demographic and baseline characteristics, the treatment effect of XIFAXAN 550 mg in reducing the risk of breakthrough overt HE recurrence was consistent for: sex, baseline Conn score, duration of current remission, and diabetes. The differences in treatment effect could not be assessed in the following subpopulations due to small sample size: non-White (n=42), baseline MELD >19 (n=26), Child-Pugh Class C (n=31), and those without concomitant lactulose use (n=26).

HE-related hospitalizations (hospitalizations directly resulting from HE, or hospitalizations complicated by HE) were reported for 19 of 140 subjects (14%) and 36 of 159 subjects (23%) in the XIFAXAN (rifaximin) and placebo groups, respectively. Comparison of Kaplan-Meier estimates of event-free curves showed XIFAXAN significantly reduced the risk of HE-related hospitalizations by 50% during the 6-month treatment period. Comparison of Kaplan-Meier estimates of event-free curves is shown in Figure 2.

Figure 2: Kaplan-Meier Event-Free Curves ^1in Pivotal HE Study (Time to First HE-Related Hospitalization in HE Study up to 6 Months of Treatment, Day 170) (ITT Population) ^2

1. Note: Open diamonds and open triangles represent censored subjects.
  ¹Event-free refers to non-occurrence of HE-related hospitalization
  ²91% of subjects were taking concomitant lactulose

Trial 2 - Risk Reduction of Hepatic Encephalopathy (XIFAXAN + lactulose vs. XIFAXAN monotherapy)

The efficacy of XIFAXAN monotherapy to reduce the risk of recurrence of overt hepatic encephalopathy was evaluated in an open-label, active-controlled, multi-center, 6-month trial of adult subjects (Trial 2). Eligible subjects had ≥1 episode of HE associated with chronic liver disease (equivalent to Conn score ≥2) in the previous 6 months.

A total of 222 subjects were randomized to receive either XIFAXAN monotherapy (550 mg twice daily) (N=113) or XIFAXAN (550 mg twice daily) + lactulose (self-titrated by the patient to produce 2 to 3 soft stools per day) (N=109). Sixty-five percent of subjects received lactulose at enrollment. Subjects randomized to XIFAXAN monotherapy who received lactulose at enrollment (N=76) discontinued lactulose on the day of randomization. Subjects had a mean age of 58 years (range, 32-85 years), 74% were <65 years of age, 63% were male, and 91% were White, 6% were Black, 1% were Asian, and 2% other.

Primary Endpoint and Results

The primary endpoint was the time to first breakthrough overt HE episode which was defined as an increase of Conn score to Grade ≥2. Breakthrough overt HE episodes occurred in 28 of 113 subjects (25%) in the XIFAXAN monotherapy group and in 15 of 109 subjects (14%) in the XIFAXAN + lactulose group during the 6-month treatment period; the hazard ratio was 1.98 (95% CI: 1.06 to 3.7). Comparison of Kaplan-Meier estimates of event-free curves showed that XIFAXAN monotherapy compared with the combination of XIFAXAN + lactulose, increased the risk of HE breakthrough by 98% during the 6-month treatment period (see Figure 3).

Figure 3. Kaplan-Meier Event-Free Curves in Trial 2 (Time to First Breakthrough HE Event up to 6 Months of Treatment, Day 170) (All Randomized Subjects)

14.3 Irritable Bowel Syndrome with Diarrhea

The efficacy of XIFAXAN for the treatment of IBS-D was established in 3 randomized, multi-center, double-blind, placebo-controlled trials in adult patients.

Trials 1 and 2 - Design

The first two trials, Trials 1 and 2 were of identical design. In these trials, a total of 1,258 patients meeting Rome II criteria for IBS* were randomized to receive XIFAXAN 550 mg three times a day (n=624) or placebo (n=634) for 14 days and then followed for a 10-week treatment-free period. The Rome II criteria further categorizes IBS patients into 3 subtypes: diarrhea-predominant IBS (IBS-D), constipation-predominant IBS (IBS-C), or alternating IBS (bowel habits alternating between diarrhea and constipation). Patients with both IBS-D and alternating IBS were included in Trials 1 and 2. XIFAXAN is recommended for use in patients with IBS-D.

*Rome II Criteria: At least 12 weeks, which need not be consecutive, in the preceding 12 months of abdominal discomfort or pain that has two out of three features:1. Relieved with defecation; and/or2. Onset associated with a change in frequency of stool; and/or3. Onset associated with a change in form (appearance) of stool.

Symptoms that Cumulatively Support the Diagnosis of Irritable Bowel Syndrome:

–Abnormal stool frequency (for research purposes “abnormal” may be defined as greater than 3 bowel movements per day and less than 3 bowel movements per week); Abnormal stool form (lumpy/hard or loose/watery stool); Abnormal stool passage (straining, urgency, or feeling of incomplete evacuation); Passage of mucus; Bloating or feeling of abdominal distension.

Trial 3 - Design

Trial 3 evaluated repeat treatment in adults with IBS-D meeting Rome III criteria** for up to 46 weeks. A total of 2,579 patients were enrolled to receive open-label XIFAXAN for 14 days. Of 2,438 evaluable patients, 1,074 (44%) responded to initial treatment and were evaluated over 22 weeks for continued response or recurrence of IBS-symptoms. A total of 636 patients had symptom recurrence and were randomized into the double-blind phase of the study. These patients were scheduled to receive XIFAXAN 550 mg three times a day (n=328) or placebo (n=308) for two additional 14-day repeat treatment courses separated by 10 weeks (see Figure 4).

Figure 4: Trial 3 Study Design

The IBS-D population from the three studies had mean age of 47 (range: 18 to 88) years of which approximately 11% of patients were ≥65 years old, 72% were female, and 88% were White.

**Rome III Criteria: Recurrent abdominal pain or discomfort (uncomfortable sensation not described as pain) at least 3 days/month in last 3 months associated with two or moreof the following: 1. Improvement with defecation; 2. Onset associated with a change in frequency of stool; 3. Onset associated with a change in form (appearance) of stool.

Trials 1 and 2 - Results

Trials 1 and 2 included 1,258 IBS-D patients (309 XIFAXAN, 314 placebo); (315 XIFAXAN, 320 placebo). The primary endpoint for both trials was the proportion of patients who achieved adequate relief of IBS signs and symptoms for at least 2 of 4 weeks during the month following 14 days of treatment. Adequate relief was defined as a response of “yes” to the following weekly Subject Global Assessment (SGA) question: “ In regards to your IBS symptoms, compared to the way you felt before you started study medication, have you, in the past 7 days, had adequate relief of your IBS symptoms? [Yes/No].”

Adequate relief of IBS symptoms was experienced by more patients receiving XIFAXAN than those receiving placebo during the month following 2 weeks of treatment (SGA-IBS Weekly Results: 41% vs. 31%, p=0.0125; 41% vs. 32%, p=0.0263 (see Table 7).

Table 5. Adequate Relief of IBS Symptoms During the Month Following Two Weeks of Treatment
Endpoint | Trial 1
Endpoint | XIFAXAN (n=309) n (%) | Placebo (n=314) n (%) | Treatment Difference (95% CI [Confidence Interval])
Adequate Relief of IBS Symptoms [The p-value for the primary endpoint for Trial 1 and for Trial 2 was <0.05] | 126 (41) | 98 (31) | 10% (2.1%, 17.1%)
Endpoint | Trial 2
Endpoint | XIFAXAN (n=315) n (%) | Placebo (n=320) n (%) | Treatment Difference (95% CI)
Adequate Relief of IBS Symptoms | 128 (41) | 103 (32) | 8% (1.0%, 15.9%)

The trials examined a composite endpoint which defined responders by IBS-related abdominal pain and stool consistency measures. Patients were monthly responders if they met both of the following criteria:

- experienced a ≥30% decrease from baseline in abdominal pain for ≥2 weeks during the month following 2 weeks of treatment
- had a weekly mean stool consistency score <4 (loose stool) for ≥2 weeks during the month following 2 weeks of treatment

More patients receiving XIFAXAN were monthly responders for abdominal pain andstool consistency in Trials 1 and 2 (see Table 8).

Table 6. Efficacy Responder Rates in Trial 1 and 2 During the Month Following Two Weeks of Treatment
Endpoint | Trial 1
Endpoint | XIFAXAN (n=309) n (%) | Placebo (n=314) n (%) | Treatment Difference (95% CI)
Abdominal Pain and Stool Consistency Respondersᵇ | 144 (47) | 121 (39) | 8% (0.3%, 15.9%)
Abdominal Pain Responders | 159 (51) | 132 (42) | 9% (1.8%, 17.5%)
Stool Consistency Responders | 244 (79) | 212 (68) | 11% (4.4%, 18.2%)
Endpoint | Trial 2
Endpoint | XIFAXAN (n=315) n (%) | Placebo (n=320) n (%) | Treatment Difference (95% CI ª)
Abdominal Pain and Stool Consistency Respondersᵇ | 147 (47) | 116 (36) | 11% (2.7%, 18.0%)
Abdominal Pain Responders | 165 (52) | 138 (43) | 9% (1.5%, 17.0%)
Stool Consistency Responders | 233 (74) | 206 (64) | 10% (2.3%, 16.7%)

ª Confidence Interval

ᵇ The p-value for the composite endpoint for Trial 1 and 2 was <0.05 and <0.01, respectively.

Trial 3 - Results

In TARGET 3, 2,579 patients were scheduled to receive an initial 14-day course of open-label XIFAXAN followed by 4 weeks of treatment-free follow-up. At the end of the follow-up period, patients were assessed for response to treatment. Patients were considered a responder if they achieved both of the following:

- ≥30% improvement from baseline in the weekly average abdominal pain score based on the daily question: “ In regards to your specific IBS symptoms of abdominal pain, on a scale of 0-10, what was your worst IBS-related abdominal pain over the last 24 hours? ‘Zero’ means you have no pain at all; ‘Ten’ means the worst possible pain you can imagine”.
- at least a 50% reduction in the number of days in a week with a daily stool consistency of Bristol Stool Scale type 6 or 7 compared with baseline where 6=fluffy pieces with ragged edges, a mushy stool; 7=watery stool, no solid pieces; entirely liquid.

Responders were then followed for recurrence of their IBS-related symptoms of abdominal pain ormushy/watery stool consistency for up to 20 treatment-free weeks.

When patients experienced recurrence of their symptoms of abdominal pain ormushy/watery stool consistency for 3 weeks of a rolling 4-week period, they were randomized into the double-blind, placebo-controlled repeat treatment phase. Of 1,074 patients who responded to open-label XIFAXAN, 382 experienced a period of symptom inactivity or decrease that did not require repeat treatment by the time they discontinued, including patients who completed the 22 weeks after initial treatment with XIFAXAN (see Figure 3).

Overall, 1,257 of 2,579 patients (49%) were nonresponders in the open-label phase and per the study protocol were withdrawn from the study. Other reasons for discontinuation include: patient request (5%), patient lost to follow-up (4%), adverse reaction (3%), and other (0.8%).

There were 1,074 (44%) of 2,438 evaluable patients who responded to initial treatment with improvement in abdominal pain andstool consistency. The response rate for each IBS symptom during the open-label phase of Trial 3 is similar to the rates seen in Trials 1 and 2 (see Table 7). A total of 636 patients subsequently had sign and symptom recurrence and were randomized to the repeat treatment phase. The median time to recurrence for patients who experienced initial response during the open-label phase with XIFAXAN was 10 weeks (range 6 to 24 weeks).

The XIFAXAN (rifaximin) and placebo treatment groups had similar baseline IBS symptom scores at the time of recurrence and randomization to the double-blind phase, but symptom scores were less severe than at study entry into the open-label phase.

Patients were deemed to have recurrent signs and symptoms by the following criteria: a return of abdominal pain or lack of stool consistency for at least 3 weeks during a 4-week follow-up period. The primary endpoint in the double-blind, placebo-controlled portion of the trial was the proportion of patients who were responders to repeat treatment in both IBS-related abdominal pain andstool consistency as defined above during the 4 weeks following the first repeat treatment with XIFAXAN. The primary analysis was performed using the worst case analysis method where patients with <4 days of diary entries in a given week are considered as non-responders for that week.

More patients receiving XIFAXAN were monthly responders for abdominal pain andstool consistency in the primary analysis in Trial 3 (see Table 9).

Table 7. Efficacy Responder Rates in Trial 3 in a Given Week for at Least 2 Weeks During Weeks 3 to 6 of the Double-Blind, First Repeat Treatment Phase
 | Placebo (n=308) n (%) | XIFAXAN (n=328) n (%) | Treatment Difference (95% CI [Confidence Intervals were derived based on CMH test adjusting for center and patients’ time to recurrence during maintenance phase])
Combined Responder [Primary endpoint] : Abdominal Pain and Stool Consistency Responders [Subjects were IBS-related abdominal pain and stool consistency responders if they were both weekly IBS-related abdominal pain responders and weekly stool consistency responders in a given week for at least 2 weeks during Weeks 3 to 6 in the double-blind first repeat treatment phase. Weekly responder in IBS-related abdominal pain was defined as a 30% or greater improvement from baseline in the weekly average abdominal pain score. Weekly responder in stool consistency was defined as a 50% or greater reduction in the number of days in a week with stool consistency of type 6 or 7 compared with baseline. The p-value for this composite endpoint was <0.05.] | 97 (31) | 125 (38) | 7% (0.9%, 16.9%)
Abdominal Pain Responders (≥30% reduction in abdominal pain) | 130 (42) | 166 (51) | 9% (1.6%, 17.0%)
Stool Consistency Responders (≥50% reduction from baseline in days/week with loose or watery stools) | 154 (50) | 170 (52) | 2% (-4.7%, 11.0%)

Thirty-six of 308 (11.7%) of placebo patients and 56 of 328 (17.1%) of XIFAXAN-treated patients responded to the first repeat treatment and did not have recurrence of signs and symptoms through the treatment-free follow-up period (10 weeks after first repeat treatment). The response rate difference was 5.4% with 95% confidence interval (1.2% to 11.6%).

16 HOW SUPPLIED/STORAGE AND HANDLING

The 550 mg tablet is a pink-colored, oval, biconvex tablet with “rfx” debossed on one side and plain on the other. It is available in the following presentations:

Bottles of approximately 360 tablets, NDC 55154-6777-8

Storage

Store XIFAXAN Tablets at 20° to 25°C (68° to 77°F); excursions permitted to 15° to 30°C (59° to 86°F) [see USP Controlled Room Temperature].

17 PATIENT COUNSELING INFORMATION

Persistent Diarrhea

For those patients being treated for travelers’ diarrhea, discontinue XIFAXAN if diarrhea persists more than 24-48 hours or worsens. Advise the patient to seek medical care for fever and/or blood in the stool [see Warnings and Precautions (5.1)].

Clostridium difficile-Associated Diarrhea

Clostridium difficile-associated diarrhea (CDAD) has been reported with use of nearly all antibacterial agents, including XIFAXAN, and may range in severity from mild diarrhea to fatal colitis. Treatment with antibiotics alters the normal flora of the colon which may lead to C. difficile. Patients can develop watery and bloody stools (with or without stomach cramps and fever) even as late as two or more months after having taken the last dose of the antibiotic. If diarrhea occurs after therapy or does not improve or worsens during therapy, advise patients to contact a physician as soon as possible [see Warnings and Precautions (5.2)].

Administration with Food

Inform patients that XIFAXAN may be taken with or without food.

Antibacterial Resistance

Counsel patients that antibacterial drugs including XIFAXAN should only be used to treat bacterial infections. They do not treat viral infections (e.g., the common cold). When XIFAXAN is prescribed to treat a bacterial infection, patients should be told that although it is common to feel better early in the course of therapy, the medication should be taken exactly as directed. Skipping doses or not completing the full course of therapy may (1) decrease the effectiveness of the immediate treatment and (2) increase the likelihood that bacteria will develop resistance and will not be treatable by XIFAXAN or other antibacterial drugs in the future [see Warnings and Precautions (5.3)].

Distributed by:

Salix Pharmaceuticals, a division of

Bausch Health US, LLC

Bridgewater, NJ 08807 USA

Patented. See https://patents.salix.comfor US patent information.

The XIFAXAN 200 mg and 550 mg products and the XIFAXAN trademark are licensed by Alfasigma S.p.A. to Salix Pharmaceuticals or its affiliates.

All other product/brand names are trademarks of the respective owners.

© 2023 Salix Pharmaceuticals, Inc. or its affiliates

Website: www.Salix.com

Distributed By:

Cardinal Health

Dublin, OH 43017

ER7970I Rev. B

9693505-70016243-02 (insert)

9693605-70016244-02 (topsert)

Package/Label Display Panel

Contains Approximately

360 Tablets

XIFAXAN®

(rifaximin) tablets

550 mg

Each tablet contains:

550 mg of rifaximin.

Pharmacist: Dispense in a tight multiple-

unit container as defined in USP.

Rx Only

WARNING: Keep out of reach of

children.